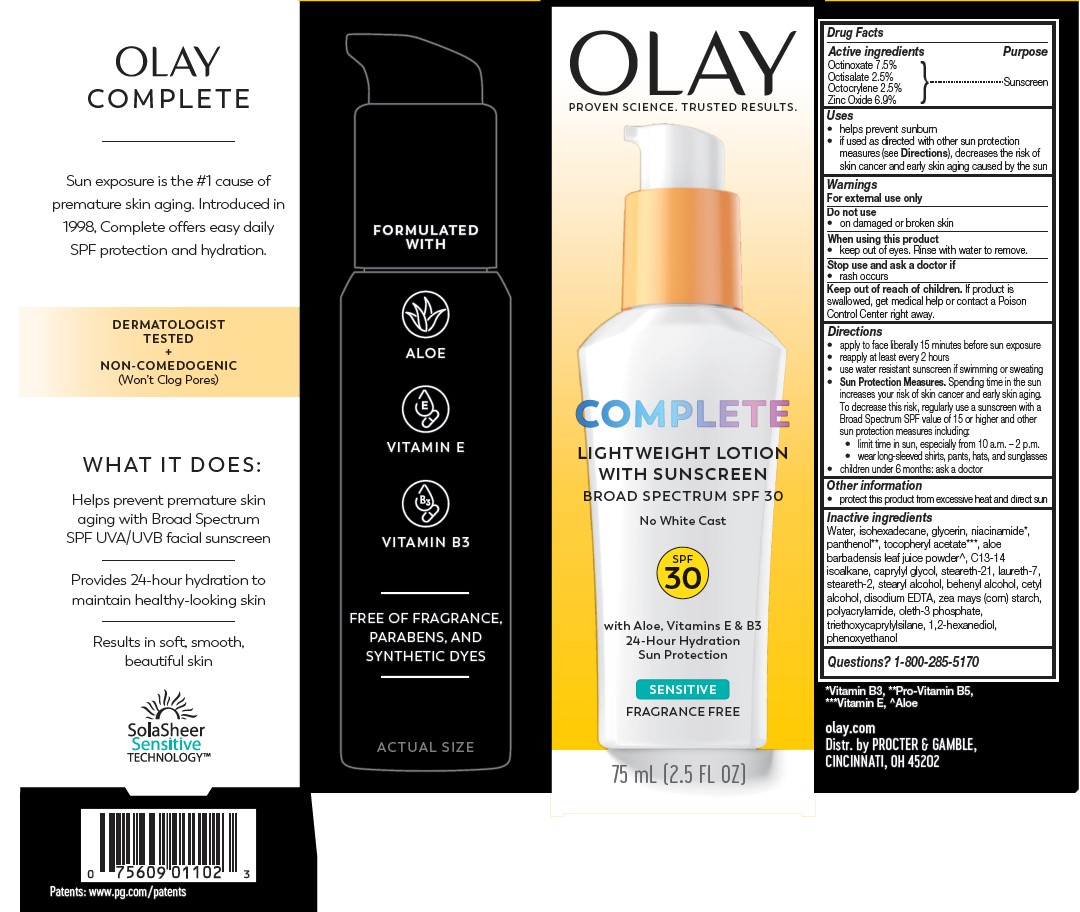 DRUG LABEL: Olay Complete Lightweight with Sunscreen Broad Spectrum SPF 30 Sensitive
NDC: 84126-163 | Form: LOTION
Manufacturer: The Procter & Gamble Manufacturing Company
Category: otc | Type: HUMAN OTC DRUG LABEL
Date: 20250819

ACTIVE INGREDIENTS: OCTINOXATE 7.5 g/100 mL; OCTISALATE 2.5 g/100 mL; OCTOCRYLENE 2.5 g/100 mL; ZINC OXIDE 6.9 g/100 mL
INACTIVE INGREDIENTS: PHENOXYETHANOL; 1,2-HEXANEDIOL; CAPRYLYL GLYCOL; POLYACRYLAMIDE (1300000 MW); ALOE VERA LEAF; ZEA MAYS (CORN) STARCH; WATER; ISOHEXADECANE; GLYCERIN; STEARETH-21; PANTHENOL; NIACINAMIDE; STEARYL ALCOHOL; BEHENYL ALCOHOL; .ALPHA.-TOCOPHEROL ACETATE; CETYL ALCOHOL; TRIETHOXYCAPRYLYLSILANE; LAURETH-7; STEARETH-2; OLETH-3 PHOSPHATE; EDETATE DISODIUM; C13-14 ISOPARAFFIN

Olay Complete Lightweight Lotion with Sunscreen Broad Spectrum SPF 30 Sensitive

PURPOSE

Sunscreen

ACTIVE INGREDIENT

Octinoxate 7.5%
Octisalate 2.5%
Octocrylene 2.5%
Zinc oxide 6.9%

Drug Facts

Uses

- helps prevent sunburn
- if used as directed with other sun protection measures (see Directions), decreases the risk of skin cancer and early skin aging caused by the sun

Warnings

For external use only

Do not use

- on damaged or broken skin

When using this product

- keep out of eyes. Rinse with water to remove.

Stop use and ask a doctor if

- rash occurs

Keep out of reach of children. If product is swallowed, get medical help or contact a Poison Control Center right away.

Directions

- apply liberally 15 minutes before sun exposure
- reapply at least every 2 hours
- use water resistant sunscreen if swimming or sweating
- Sun Protection Measures. Spending time in the sun increases your risk of skin cancer and early skin aging. To decrease this risk, regularly use a sunscreen with a Broad Spectrum SPF value of 15 or higher and other sun protection measures including:
  - limit time in sun, especially from 10 a.m. - 2 p.m.
  - wear long-sleeved shirts, pants, hats, and sunglasses
- children under 6 months: ask a doctor

Other information

- protect this product from excessive heat and direct sun

Inactive ingredients

Water, isohexadecane, glycerin, niacinamide, panthenol, tocopheryl acetate, aloe barbadensis leaf juice powder, C13-14 isoalkane, caprylyl glycol, steareth-21, laureth-7, steareth-2, stearyl alcohol, behenyl alcohol, cetyl alcohol, disodium EDTA, zea mays (corn) starch, polyacrylamide, oleth-3 phosphate, triethoxycaprylylsilane, 1,2-hexanediol, phenoxyethanol

Questions or comments?

Call 1-800-285-5170

Distr. by
PROCTER & GAMBLE,
CINCINNATI, OH 45202

PACKAGE LABEL

OLAY

COMPLETE

LIGHTWEIGHT LOTION

WITH SUNSCREEN

BROAD SPECTRUM SPF 30

SENSITIVE

FRAGRANCE FREE

75 mL (2.5 FL OZ)